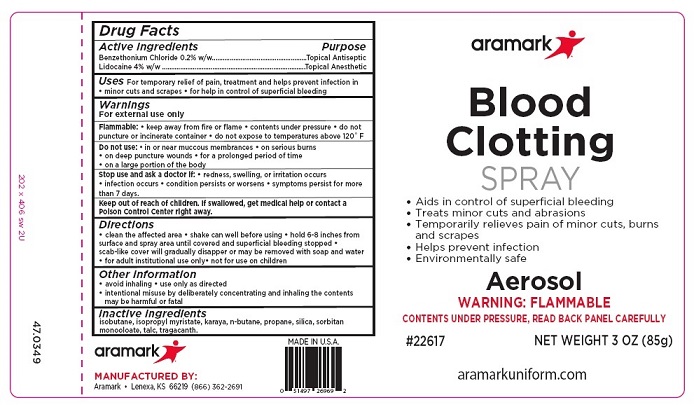 DRUG LABEL: Aramark Blood Clotting
NDC: 81238-2106 | Form: SPRAY
Manufacturer: Western First Aid Safety dba Aramark
Category: otc | Type: HUMAN OTC DRUG LABEL
Date: 20210629

ACTIVE INGREDIENTS: LIDOCAINE 3400 mg/85 g; BENZETHONIUM CHLORIDE 170 mg/85 g
INACTIVE INGREDIENTS: ISOBUTANE; ISOPROPYL MYRISTATE; KARAYA GUM; BUTANE; PROPANE; SILICON DIOXIDE; 3-(TRIETHOXYSILYL)PROPYLAMINE; SORBITAN MONOOLEATE; TALC; TRAGACANTH

Aramark Blood Clotting Spray

Active Ingredients

Benzethonium Chloride 0.2% w/w
Lidocaine 4% w/w

Purpose

Benzethonium Chloride ...Topical Antiseptic
Lidocaine ....................Topical Anisthetic

INDICATIONS AND USAGE

Uses For temporary relief of pain, treatment and helps prevent infection in
• minor cuts and scrapes • for help in control of superficial bleeding

Warnings

For external use only
Flammable: • keep away from fire or flame • contents under pressure • do not
puncture or incinerate container • do not expose to temperatures above 120 F

Do not use: • in or near muccous membrances • on serious burns
• on deep puncture wounds • for a prolonged period of time
• on a large portion of the body

Stop use and ask a doctor if: • redness, swelling, or irritation occurs
• infection occurs • condition persists or worsens • symptoms persist for more
than 7 days.

Keep out of reach of children. If swallowed, get medical help or contact a
Poison Control Center right away.

Directions
• clean the affected area • shake can well before using • hold 6-8 inches from
surface and spray area until covered and superficial bleeding stopped •
scab-like cover will gradually disappear or may be removed with soap and water
• for adult institutional use only• not for use on children

Other Information
• avoid inhaling • use only as directed
• intentional misuse by deliberately concentrating and inhaling the contents
may be harmful or fatal

Inactive Ingredients

1sobutane, 1sopropyl myristate, karaya, n-butane, propane, silica, silicone, sorbitan

monooleate, talc, tragacanth

Principal Display

aramark

Blood
Clotting
SPRAY

• Aids in control of superficial bleeding
• Treats minor cuts and abrasions
• Temporarily relieves pain of minor cuts, burns
and scrapes
• Helps prevent infection
• Environmentally safe

Aerosol
WARNING: FLAMMABLE
CONTENTS UNDER PRESSURE, READ BACK PANEL CAREFULLY

#22617 NET WEIGHT 3 OZ (85g)

MANUFACTURED BY:

Aramark • Lenexa, KS 66219 (866) 362-2691

aramarkuniform.com

res